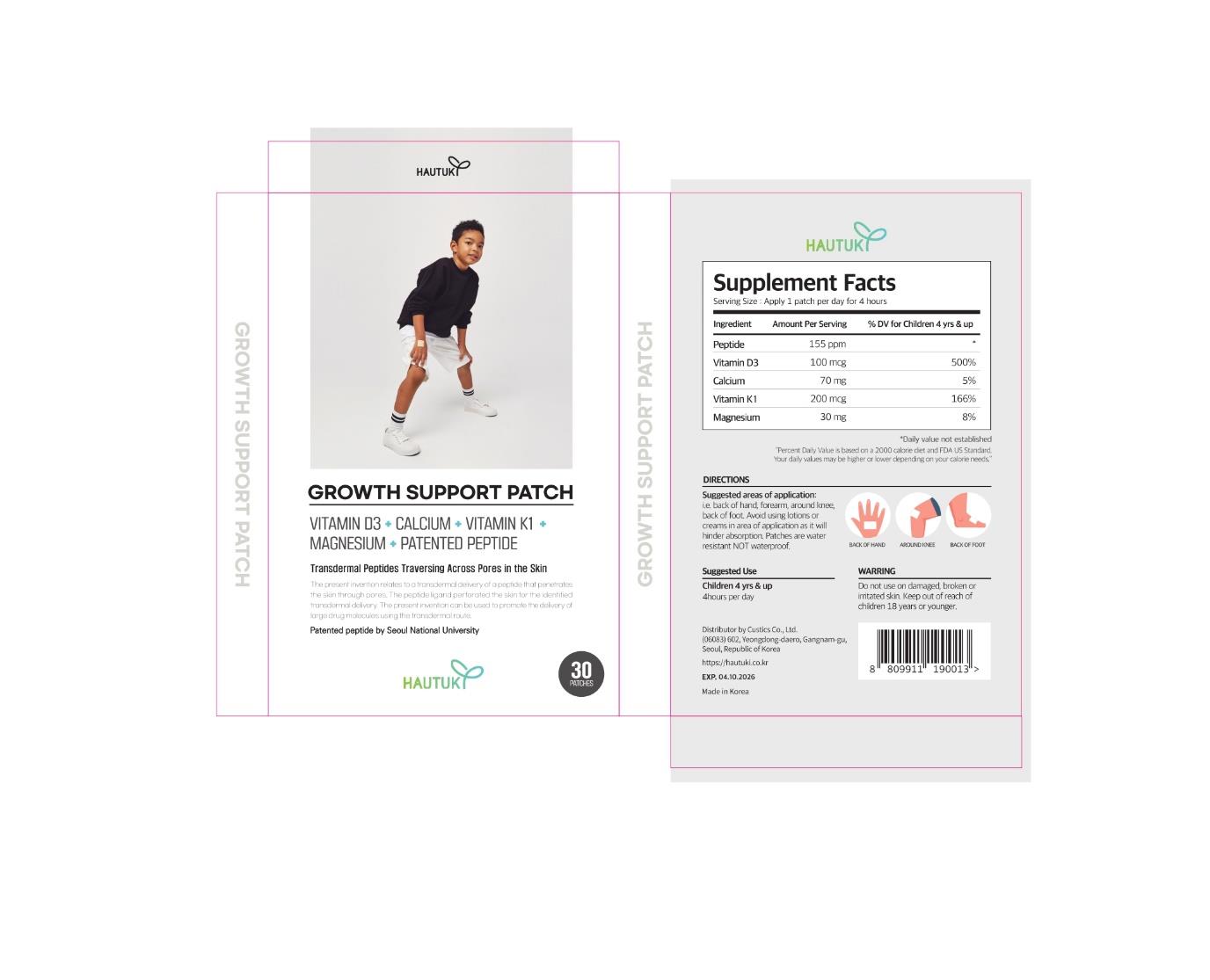 DRUG LABEL: GROWTH SUPPORTPATCH, HAUTUKI
NDC: 83463-0002 | Form: PATCH
Manufacturer: CUSTICS
Category: otc | Type: HUMAN OTC DRUG LABEL
Date: 20230522

ACTIVE INGREDIENTS: CHOLECALCIFEROL 0.2 mg/100 g
INACTIVE INGREDIENTS: CALCIUM LACTATE; MAGNESIUM CHLORIDE; PHYTONADIONE; MINERAL OIL

Drug Facts

ACTIVE INGREDIENT

Capsicum annuum extract

INACTIVE INGREDIENT

Hydrogenated Dicyclopentadiene/Isopentene/Isoprene/Styrene Copolymer (and) Mineral Oil (and) Hydrogenated Styrene/Butadiene Copolymer, coffee seed extract, soil mineral, cordycepin

PURPOSE

It delivers nutrients such as vitamins in the patch to the body.

keep out of reach of the children

INDICATIONS AND USAGE

Use 1 patch per day (* 4hours per day). Children 4yrs & up. i.e back of hand, forearm, around knee,
back of foot. Avoid using lotion or creams in area of application as it will hinder absorption. Patchs
are water resistant NOT waterproof.

Do not use on damaged, broken or irritated skin. Keep out of reach of children 18 years or younger.

DOSAGE AND ADMINISTRATION

for external use only